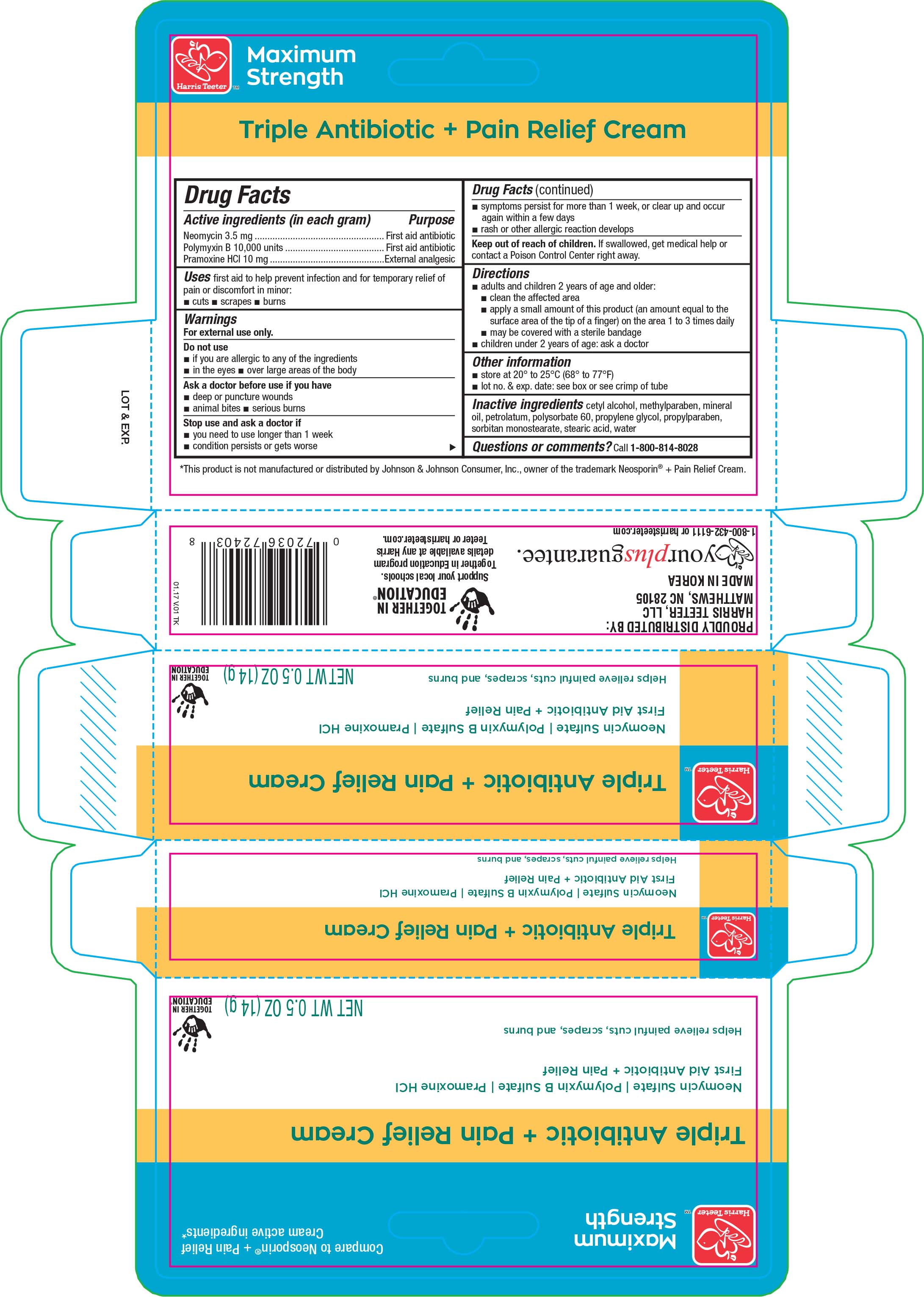 DRUG LABEL: Harris Teeter Triple Antibiotic Plus Pain Relief
NDC: 72036-403 | Form: CREAM
Manufacturer: Harris Teeter
Category: otc | Type: HUMAN OTC DRUG LABEL
Date: 20170420

ACTIVE INGREDIENTS: NEOMYCIN SULFATE 3.5 mg/1 g; POLYMYXIN B SULFATE 10000 [USP'U]/1 g; PRAMOXINE HYDROCHLORIDE 10 mg/1 g
INACTIVE INGREDIENTS: CETYL ALCOHOL; METHYLPARABEN; MINERAL OIL; PETROLATUM; POLYSORBATE 60; PROPYLENE GLYCOL; PROPYLPARABEN; SORBITAN MONOSTEARATE; STEARIC ACID; WATER

Active ingredients (in each gram) Purpose

Neomycin 3.5 mg..................................................................First aid antibiotic

Polymyxin B 10,000 units.......................................................First aid antibiotic

Pramoxine HCI 10 mg............................................................External analgesic

PURPOSE

Uses first aid to help prevent infection and for temporary relief of pain or discomfort in minor:

- cuts
- scrapes
- burns

Warnings

For external use only.

Do not use

- if you are allergic to any of the ingredients
- in the eyes
- over large areas of the body

Ask a doctor before use if you have

- deep or puncture wounds
- animal bites
- serious burns

Stop use and ask a doctor if

- you need to use longer than 1 week
- condition persists or gets worse
- symptoms persist for more than 1 week, or clear up, and occur again within a few days
- rash or other allergic reaction develops

Keep out of reach of children. If swallowed, get medical help or contact a Poison Control Center right away.

Directions

- adults and children 2 years of age and older:
- clean the affected area
- apply a small amount of this product (an amount equal to the surface area of the tip of a finger) on the area 1 to 3 times daily
- may be covered with a sterile bandage
- children under 2 years of age: ask a doctor

Other information

- store at 20° to 25°C (68° to 77°F)
- lot no. & exp. date: see box or see crimp of tube

Inactive ingredients

- cetyl alcohol, methylparaben, mineral oil, petrolatum, polysorbate 60, propylene glycol, propylparaben, sorbitan monostearate, stearic acid, water

DOSAGE AND ADMINISTRATION

Distributed by:

Harris Teeter, LLC

Matthews, NC 28105

Made in Korea